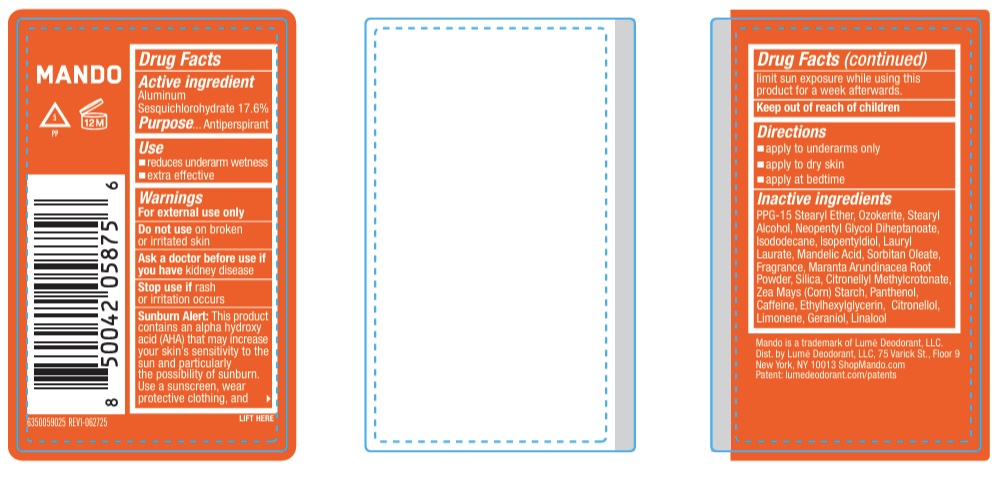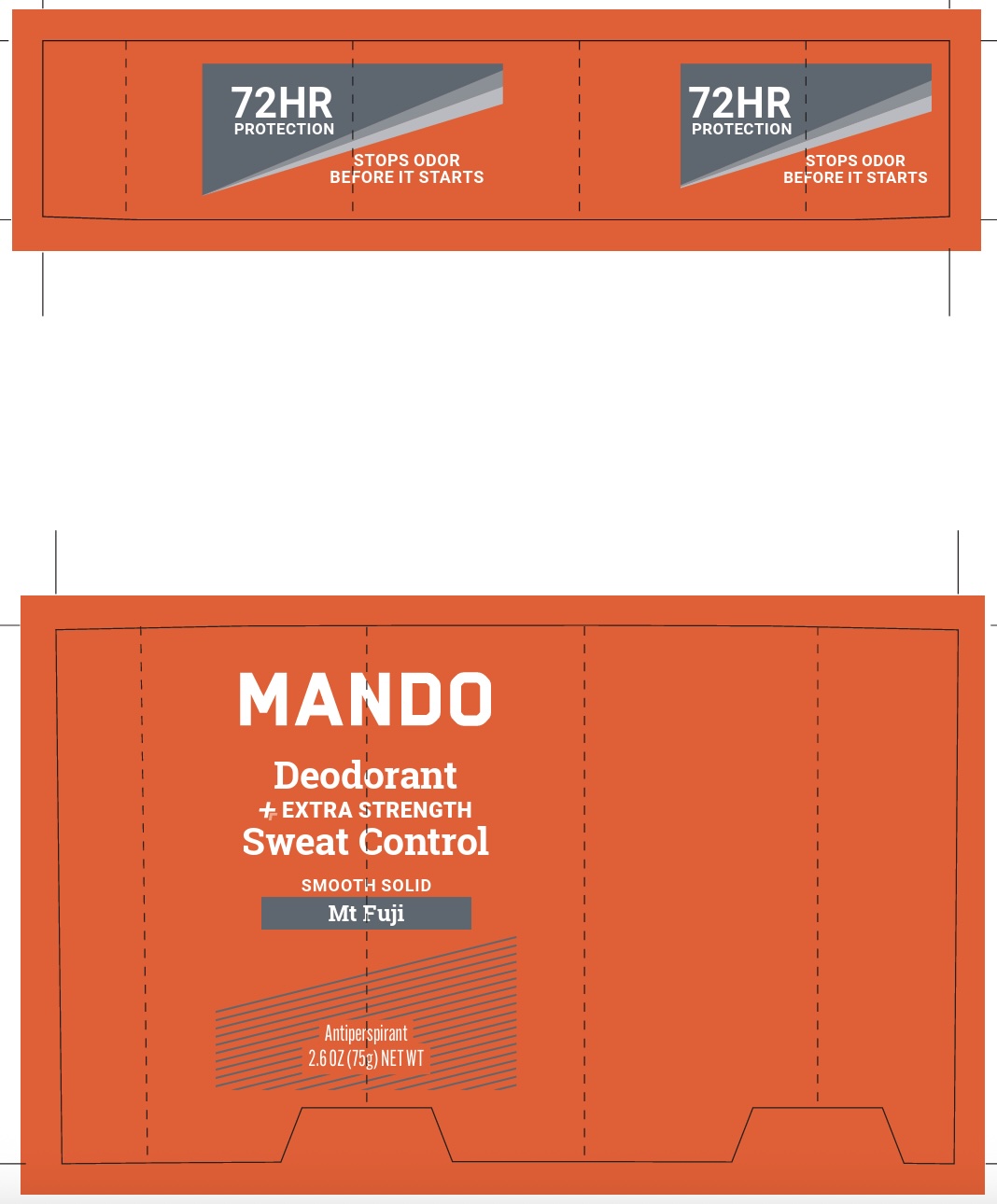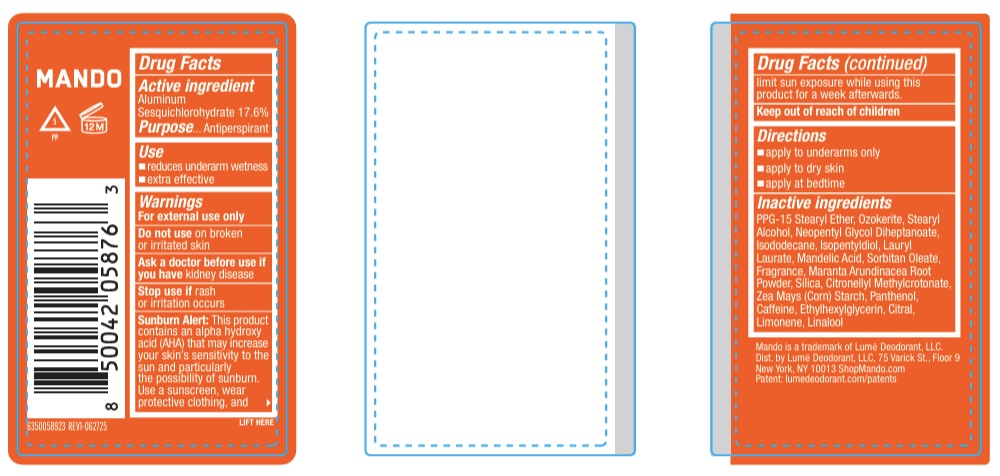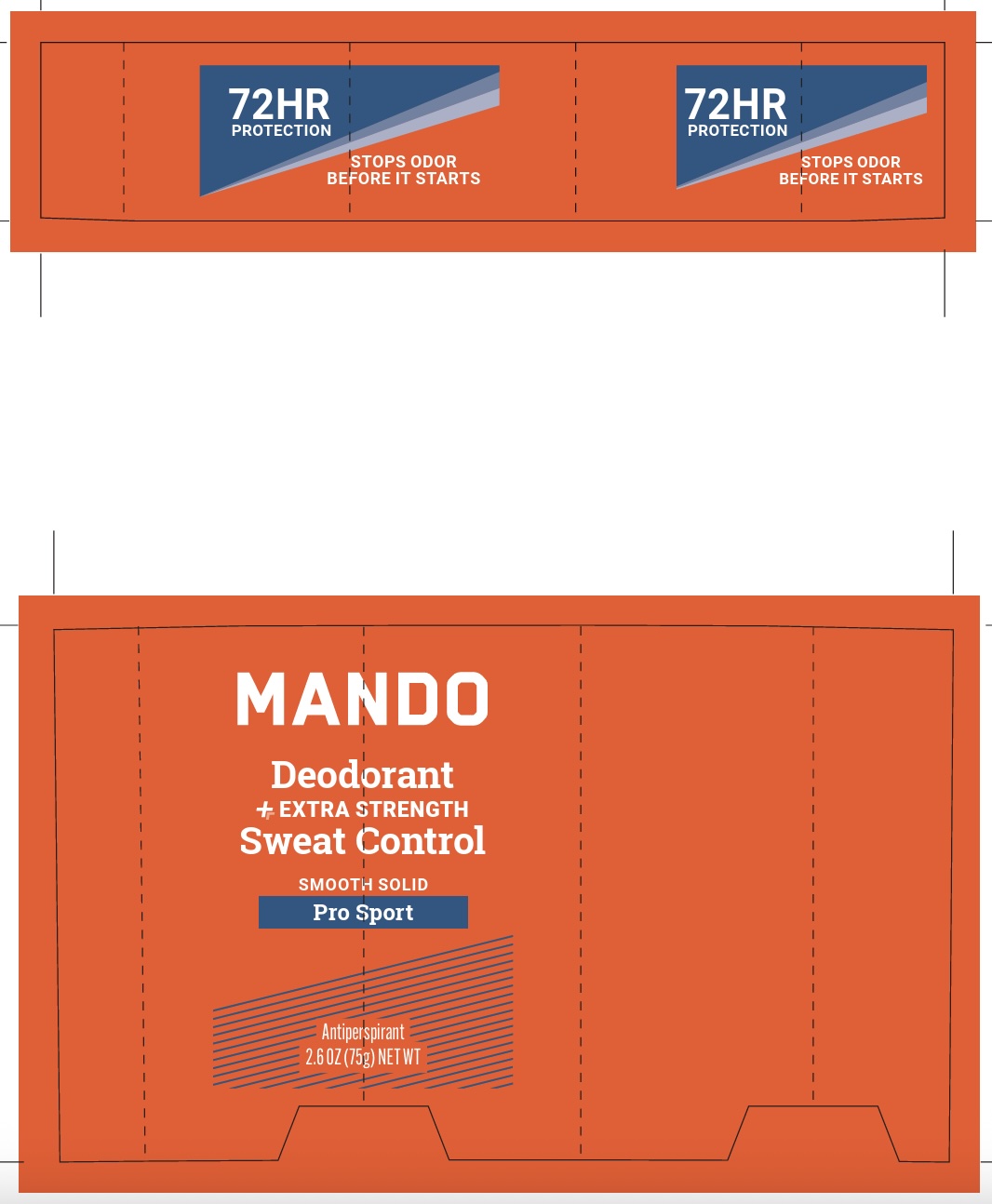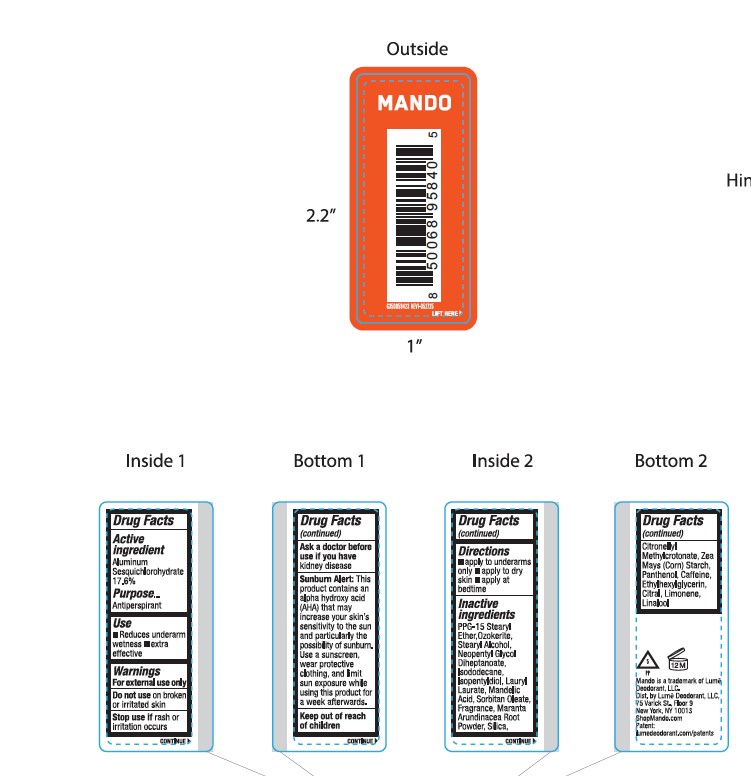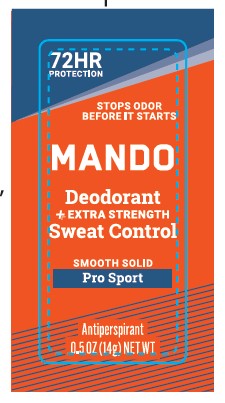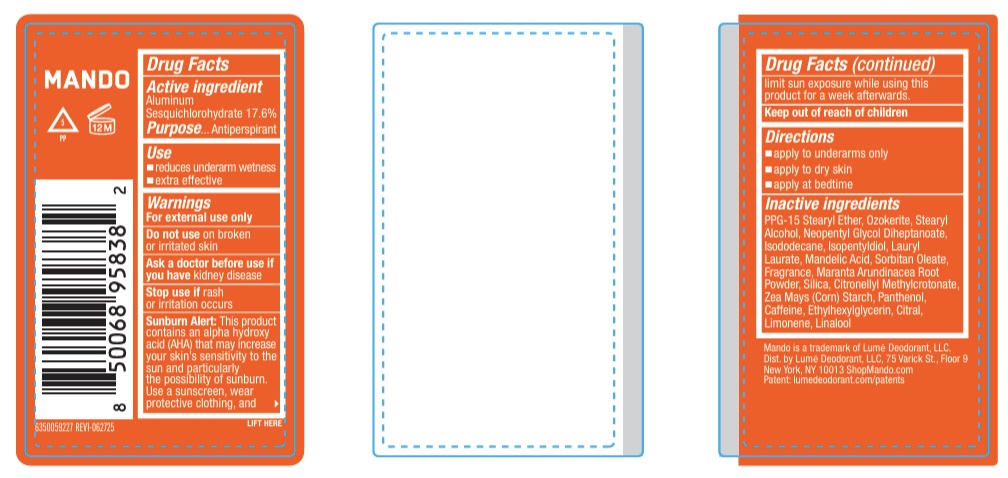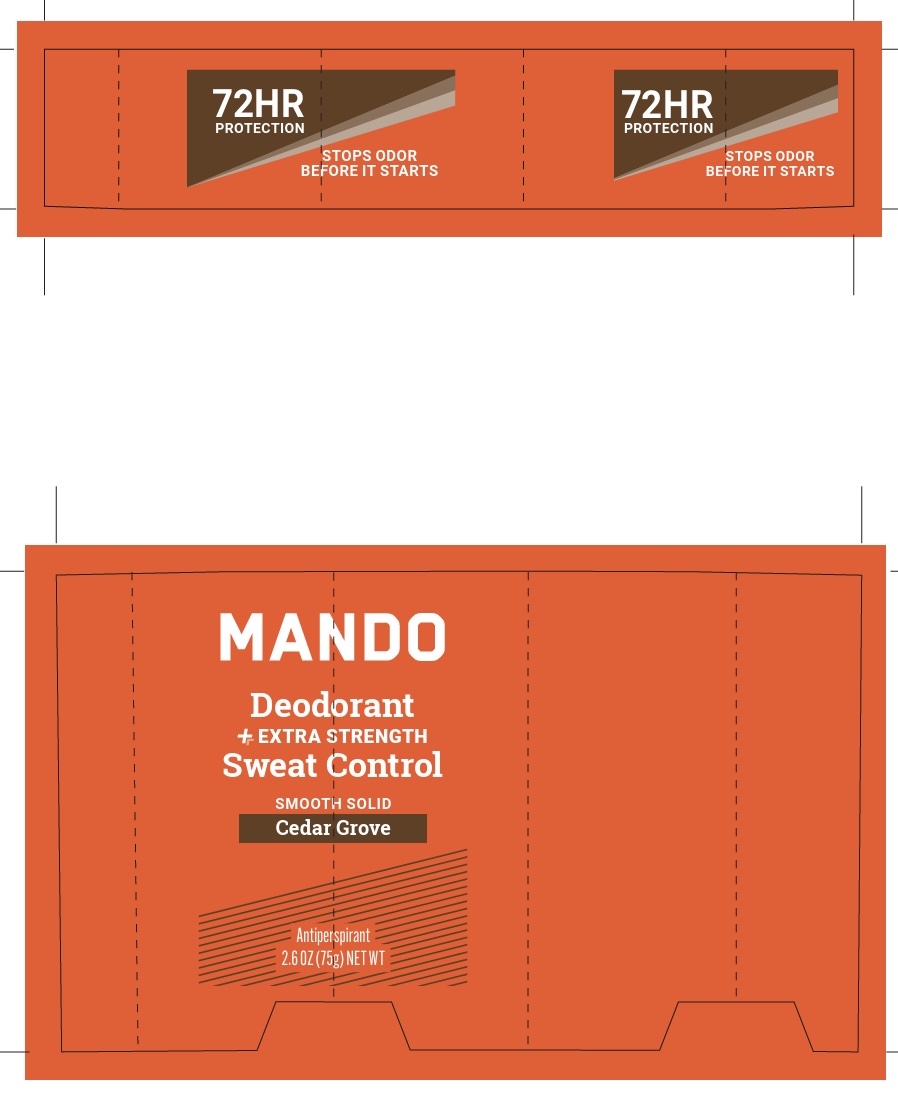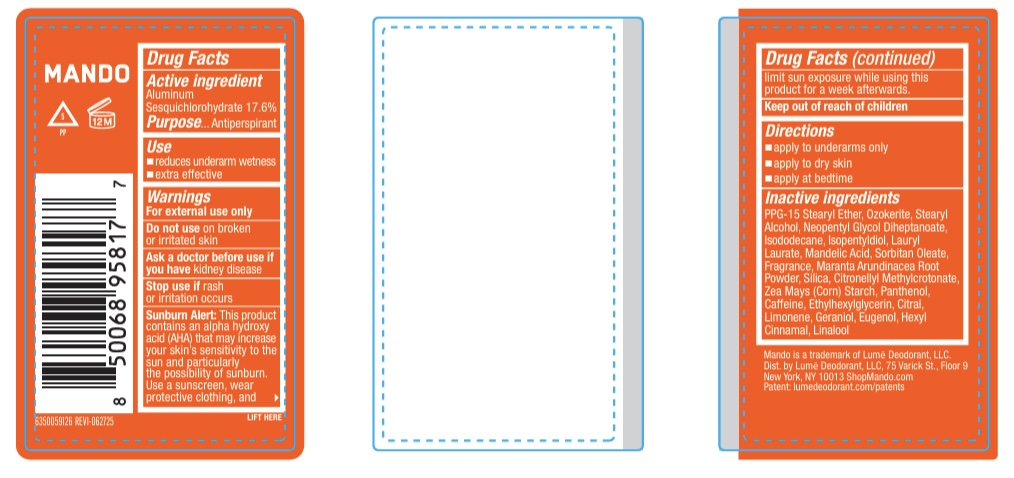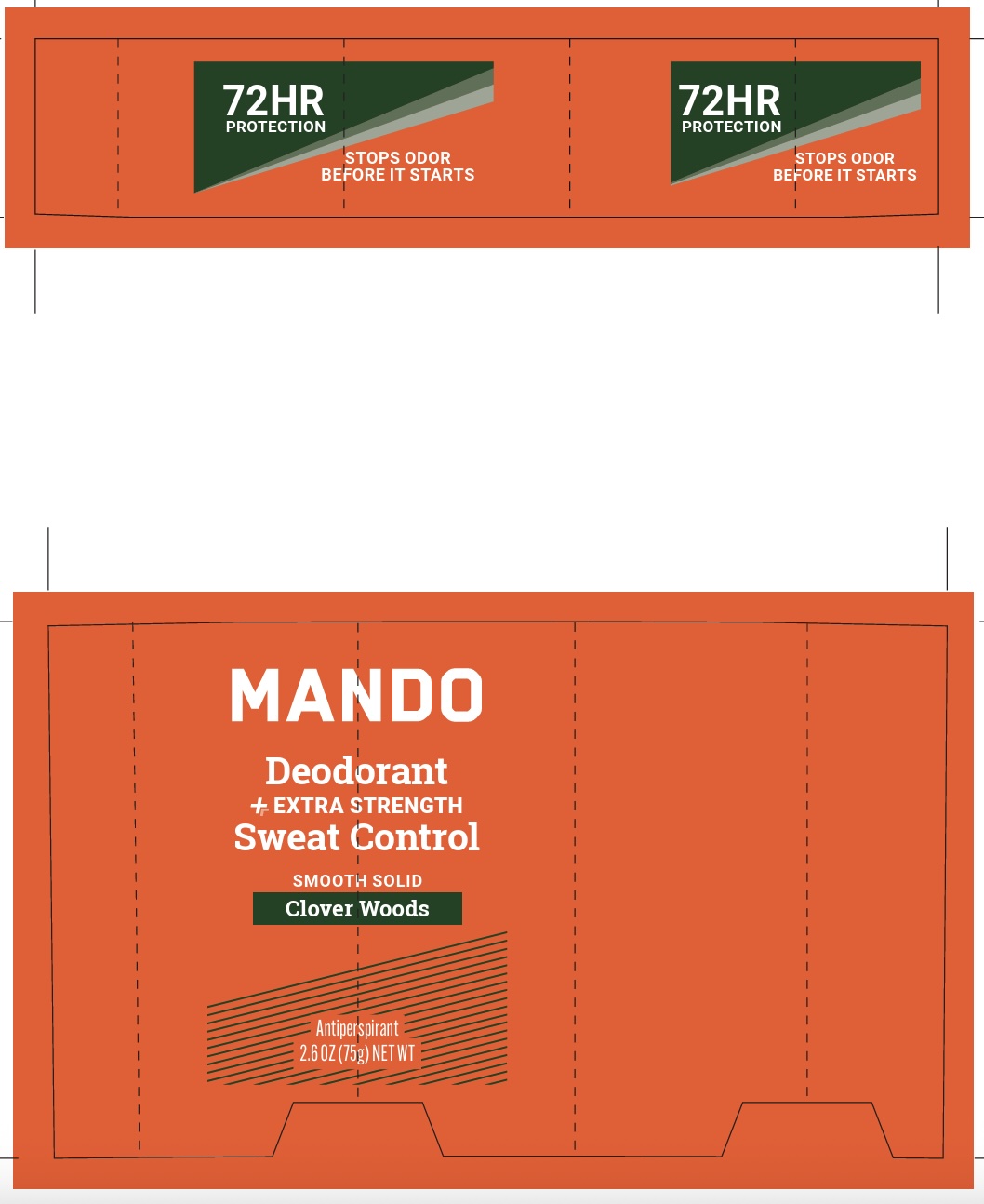 DRUG LABEL: Mando - Mt. Fuji
NDC: 84520-005 | Form: STICK
Manufacturer: Lume Deodorant, LLC.
Category: otc | Type: HUMAN OTC DRUG LABEL
Date: 20260114

ACTIVE INGREDIENTS: ALUMINUM SESQUICHLOROHYDRATE 13.2 g/75 g
INACTIVE INGREDIENTS: LIMONENE, (+)-; CERESIN; SORBITAN OLEATE; CITRONELLOL; LINALOOL, (+)-; GERANIOL; NEOPENTYL GLYCOL DIHEPTANOATE; MANDELIC ACID; CITRONELLYL METHYLCROTONATE; FRAGRANCE 13576; MARANTA ARUNDINACEA ROOT; ETHYLHEXYLGLYCERIN; PPG-15 STEARYL ETHER; STEARYL ALCOHOL; ISODODECANE; ISOPENTYLDIOL; CAFFEINE; LAURYL LAURATE; PANTHENOL; STARCH, CORN; SILICON DIOXIDE

Mando Deodorant

ACTIVE INGREDIENT

Aluminum Sesquichlorohydrate 17.6%

PURPOSE

Antiperspirant

USE

- reduces underarm wetness
- extra effective

WARNINGS

For external use only

Do not use on broken or irritated skin

Ask a doctor before use if you have kidney disease

Stop use if rash or irritation occurs

Sunburn Alert: This product contains an alpha hydroxy acid (AHA) that may increase your skin’s sensitivity to the sun and particularly the possibility of sunburn. Use a sunscreen, wear protective clothing, and limit sun exposure while using this product for a week afterwards.

KEEP OUT OF REACH OF CHILDREN

DIRECTIONS

- apply to underarms only
- apply to dry skin
- apply at bedtime

INACTIVE INGREDIENTS

PPG-15 Stearyl Ether, Neopentyl Glycol Diheptanoate, Stearyl Alcohol, Isododecane, Isopentyldiol, Lauryl Laurate, Mandelic Acid, Sorbitan Monooleate / Oleate, Maranta Arundinacea Root / Powder, Silicon Dioxide / Silica, Citronellyl Methylcrotonate, Zea Mays (Corn) Starch, Ethylhexylglycerin, Fragrance / Parfum, Panthenol, Caffeine, Limonene